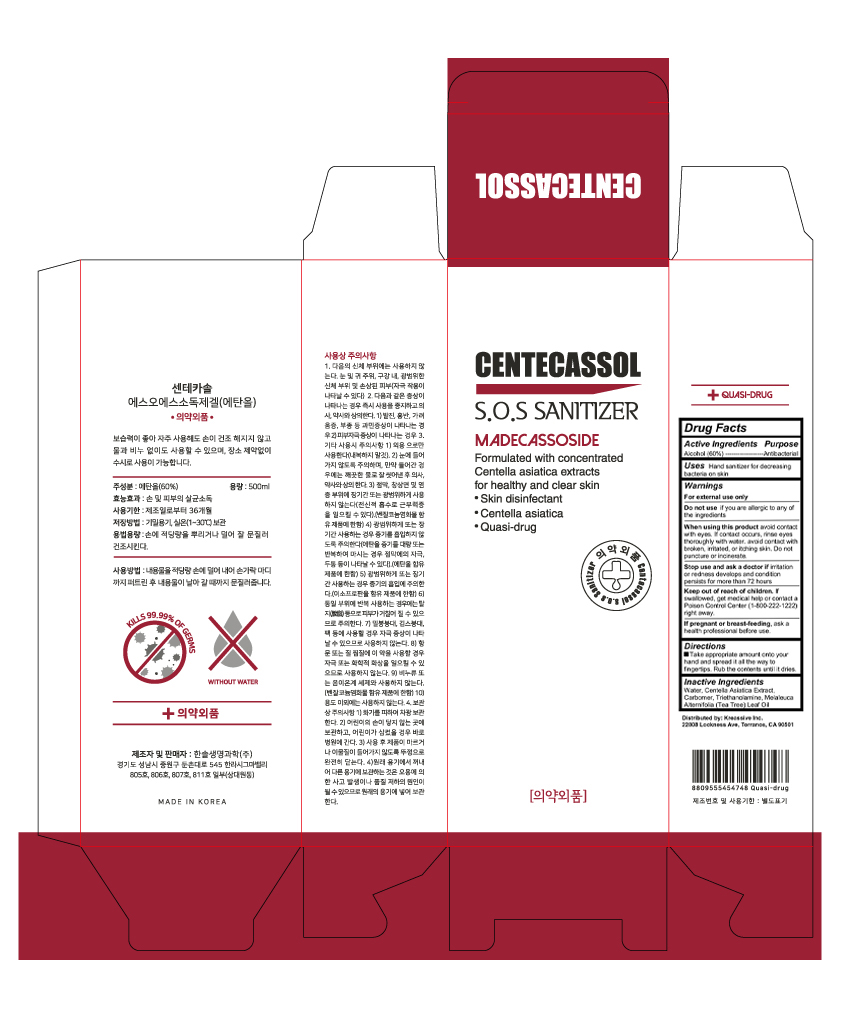 DRUG LABEL: CENTECASSOL S.O.S SANITIZER
NDC: 73800-102 | Form: GEL
Manufacturer: HANSOLBIO CO., LTD
Category: otc | Type: HUMAN OTC DRUG LABEL
Date: 20200410

ACTIVE INGREDIENTS: ALCOHOL 60 mL/100 mL
INACTIVE INGREDIENTS: WATER; CENTELLA ASIATICA WHOLE; TROLAMINE; TEA TREE OIL

CENTECASSOL S.O.S SANITIZER

Active ingredient

Alcohol (60%)

Purpose

Antibacterial

Uses

Uses Hand sanitizer for decreasing bacteria on skin

Warnings

For external use only

Do not use if you are allergic to any of the ingredients

When using this product avoid contact with eyes. If contact occurs, rinse eyes thoroughly with water. avoid contact with broken, irritated, or itching skin. Do not puncture or incinerate.

Stop use and ask a doctor ifirritation or redness develops and condition persists for more than 72 hours

If pregnant or breast-feeding, ask a health professional before use.

Directions

Take appropriate amount onto your hand and spread it all the way to fingertips. Rub the contents until it dries

Keep out of reach of children

If swallowed, get medical help or contact a Poison Control Center (1-800-222-1222) right away.

Inactive ingredients

Water, Centella Asiatica Extract, Carbomer, Triethanolamine, Melaleuca Alternifolia (Tea Tree) Leaf Oil